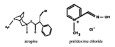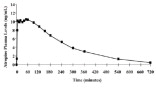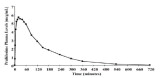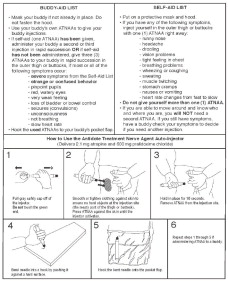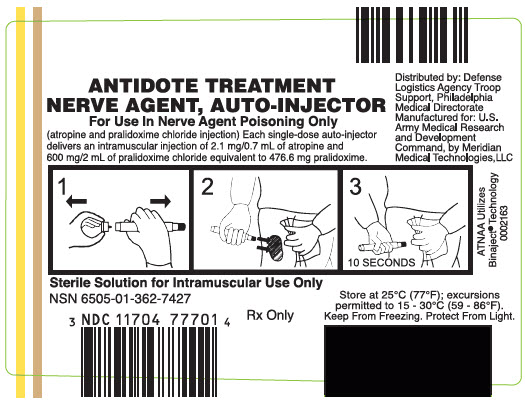 DRUG LABEL: ATNAA atropine and pralidoxime chloride 
NDC: 11704-777 | Form: KIT | Route: INTRAMUSCULAR
Manufacturer: Meridian Medical Technologies, LLC
Category: prescription | Type: HUMAN PRESCRIPTION DRUG LABEL
Date: 20220718

ACTIVE INGREDIENTS: atropine 2.1 mg/0.7 mL; pralidoxime chloride 600 mg/2 mL
INACTIVE INGREDIENTS: Glycerin; Citric Acid Monohydrate; Phenol; Water; Sodium Citrate, Unspecified Form; Nitrogen; Benzyl Alcohol; Glycine; Water; Hydrochloric Acid

HIGHLIGHTS OF PRESCRIBING INFORMATION

These highlights do not include all the information needed to use ATNAA safely and effectively. See full prescribing information for ATNAA.
ATNAA (atropine and pralidoxime chloride injection), for intramuscular use
Initial U.S. Approval: 2002

1 INDICATIONS AND USAGE

ATNAA, a combination of atropine, a cholinergic muscarinic antagonist, and pralidoxime chloride, a cholinesterase reactivator, is indicated for the treatment of poisoning by susceptible organophosphorus nerve agents having anticholinesterase activity in adults. (1)

2 DOSAGE AND ADMINISTRATION

- ATNAA is intended as an initial treatment as soon as symptoms appear; definitive medical care should be sought immediately. (2.1)
- Dosage for Mild Symptoms: If a service member experiences some or all of the mild symptoms, they should self-administer one injection intramuscularly into the lateral thigh muscle or buttocks. If, at any time after the first dose, the service member develops any of the severe symptoms or if the mild symptoms are not relieved, a buddy should administer two additional injections intramuscularly in rapid succession. (2.2)
- Dosage for Severe Symptoms: If a service member has any of the severe symptoms, immediately buddy-administer three injections intramuscularly into the service member's lateral thigh muscle or buttocks in rapid succession. (2.2)

3 DOSAGE FORMS AND STRENGTHS

Injection: Each single-dose ATNAA autoinjector contains atropine (2.1 mg/0.7 mL) plus pralidoxime chloride (600 mg/2 mL). (3)

4 CONTRAINDICATIONS

None. (4)

5 WARNINGS AND PRECAUTIONS

- Cardiovascular (CV) Risks: Tachycardia, palpitations, premature ventricular contractions, flutter, fibrillation, etc. Use caution in individuals with known CV disease or conduction problems. (5.1)
- Heat Injury: May inhibit sweating and lead to hyperthermia; avoid excessive exercising and heat exposure. (5.2)
- Acute Glaucoma: May precipitate in susceptible individuals. (5.3)
- Urinary Retention: Administer with caution in individuals with bladder outflow obstruction. (5.4)
- Pyloric Stenosis: May convert into complete obstruction. (5.5)
- Exacerbation of Chronic Lung Disease: Atropine may cause inspiration of bronchial secretions and formation of dangerous viscid plugs in individuals with chronic lung disease; monitor respiratory status. (5.6)

6 ADVERSE REACTIONS

Common adverse reactions of atropine include dryness of mouth, blurred vision, dry eyes, photophobia, confusion, headache, and dizziness among others. (6.1) The common adverse reactions of pralidoxime chloride include changes in vision, dizziness, headache, drowsiness, nausea, tachycardia, increased blood pressure, muscular weakness, dry mouth, emesis, rash, dry skin, hyperventilation, decreased renal function, excitement, manic behavior, and transient elevation of liver enzymes and creatine phosphokinase. (6.2)

To report SUSPECTED ADVERSE REACTIONS, contact Meridian Medical Technologies®, LLC at 1-833-739-0945 or FDA at 1-800-FDA-1088 or www.fda.gov/medwatch.

7 DRUG INTERACTIONS

- Succinylcholine and Mivacurium: Accelerated reversal of neuromuscular blocking effects may occur; monitor with concomitant administration. (7.1)

8 USE IN SPECIFIC POPULATIONS

- Geriatric individuals may be more susceptible to the effects of atropine. (8.5)

FULL PRESCRIBING INFORMATION

1 INDICATIONS AND USAGE

ATNAA is indicated for the treatment of poisoning by susceptible organophosphorus nerve agents having anticholinesterase activity in adults.

2 DOSAGE AND ADMINISTRATION

2.1 Important Administration Information

- Three (3) ATNAA single-dose autoinjectors should be available for use by each service member at risk for organophosphorus nerve agent poisoning; one (1) for mild symptoms plus two (2) more for severe symptoms [see Dosage and Administration (2.2)]. Note that individuals may not have all symptoms included under the mild or severe symptom category.
- For optimal reactivation of organophosphorus-inhibited cholinesterase, the ATNAA should be administered as soon as possible after appearance of symptoms of organophosphorus nerve agent poisoning.
- ATNAA should be self- or buddy–administered by service members after donning protective mask and hood at the first sign of a chemical attack, and only if some or all of the mild symptoms of organophosphorus nerve agent exposure are present.
- Only administer ATNAA to service members experiencing symptoms of organophosphorus nerve agent poisoning in a situation where exposure is known or suspected. The ATNAA autoinjector is intended as an initial treatment of the symptoms of organophosphorus nerve agent poisoning as soon as symptoms appear; definitive medical care should be sought immediately.
- Close supervision of all treated service members is indicated for at least 48 to 72 hours.
- Parenteral drug products should be inspected visually for particulate matter and discoloration prior to administration, whenever solution and container permit [see Dosage Forms and Strengths (3)].

2.2 Dosage Information

Dosage for Mild Symptoms

First Dose: If you experience some or all of the mild symptoms of nerve agent exposure listed in Table 1, self-administer one (1) ATNAA injection intramuscularly into the lateral thigh muscle or buttocks.

Wait 10 to 15 minutes for ATNAA to take effect. If, after 10 to 15 minutes, the symptoms of organophosphorus nerve agent poisoning are not relieved, seek someone else to check your symptoms. Another service member must administer the second and third injections.

Additional Doses: If you encounter a service member suffering from severe symptoms of organophosphorus nerve agent poisoning listed in Table 1 and one ATNAA has been self-administered, administer two (2) additional ATNAA injections intramuscularly in rapid succession into the casualty's lateral thigh muscle or buttocks.

Dosage for Severe Symptoms

Casualties with severe symptoms may experience most or all of the mild symptoms of organophosphorus nerve agent poisoning, plus most or all of the severe symptoms listed in Table 1.

If a service member is encountered suffering from severe signs of organophosphorus nerve agent poisoning and ATNAA self-aid has not been administered, immediately administer in rapid succession three (3) ATNAA injections into the casualty's lateral thigh muscle or buttocks.

Table 1. Common Symptoms of Organophosphorus Nerve Agent Exposure
Mild Symptoms | Severe Symptoms
- Unexplained runny nose - Unexplained sudden headache - Sudden drooling - Difficulty in seeing (dimness of vision and miosis) - Tightness of chest or difficulty in breathing - Wheezing and coughing - Localized sweating and muscular twitching in the area of contaminated skin - Stomach cramps - Nausea, with or without vomiting - Tachycardia followed by bradycardia | - Strange or confused behavior - Increased wheezing and increased difficulty in breathing - Severely pinpointed pupils - Red eyes with tearing - Vomiting - Severe muscular twitching and general weakness - Involuntary urination and defecation - Convulsions - Unconsciousness - Respiratory failure - Bradycardia

2.3 Administration Instructions

The following instructions should be given to service members for the administration of ATNAA single-dose injections.

Self-Aid

1. Administer one (1) ATNAA into your lateral thigh muscle or buttocks as follows:
  1. Remove gray safety cap from back end.
  2. Place front end on outer thigh and push hard until injector functions. Hold firmly in place for ten seconds.
  3. Using a hard surface, bend needle into hook. Push ejected needle through a pocket flap (or other thick and conspicuous part of outer clothing).
2. Wait 10 to 15 minutes for the antidote to take effect. If you are able to ambulate, know who you are, and where you are, you will NOT need a second injection.
  Giving yourself a second set of injections may cause an overdose of the ATNAA which could result in incapacitation.
3. If symptoms of organophosphorus nerve agent poisoning are not relieved after administering one injection, seek someone else to check your symptoms. A buddy must administer the second and third injections, if needed.

Buddy-Aid

If you encounter a service member suffering from any of the severe symptoms of organophosphorus nerve agent poisoning, render the following aid:

1. Mask the casualty, if necessary. Do not fasten the hood.
2. If self-aid (one ATNAA injection) has been administered, administer in rapid succession two (2) additional ATNAA injections into the casualty's lateral thigh muscle or buttocks.
  Use the casualty's own ATNAAs when providing aid. Do not use your own autoinjectors on a casualty. If you do, you may not have any antidote available when needed for self-aid.
3. If self-aid (one ATNAA injection) has not been administered, administer in rapid succession three (3) ATNAA injections into the casualty's lateral thigh muscle or buttocks.

3 DOSAGE FORMS AND STRENGTHS

Injection: Each single-dose ATNAA autoinjector contains the following in two separate chambers:

- front chamber (visible): a clear, colorless to yellow, sterile solution of atropine (2.1 mg/0.7 mL)
- back chamber (not visible): a clear, colorless to yellow, sterile solution of pralidoxime chloride (600 mg/2 mL) equivalent to pralidoxime (476.6 mg/2 mL)

When activated, ATNAA sequentially administers both drugs intramuscularly through a single needle in one injection.

4 CONTRAINDICATIONS

None.

5 WARNINGS AND PRECAUTIONS

5.1 Cardiovascular Risks

Cardiovascular adverse reactions reported in the literature for atropine include, but are not limited to, sinus tachycardia, palpitations, premature ventricular contractions, atrial flutter, atrial fibrillation, ventricular flutter, ventricular fibrillation, cardiac syncope, asystole, and myocardial infarction. In individuals with a recent myocardial infarction and/or severe coronary artery disease, there is a possibility that atropine-induced tachycardia may cause ischemia, extend or initiate myocardial infarcts, and stimulate ventricular ectopy and fibrillation. ATNAA should be used with caution in individuals with known cardiovascular disease or cardiac conduction problems.

5.2 Heat Injury

Atropine may inhibit sweating which, in a warm environment or with excessive exercise, can lead to hyperthermia and heat injury. To the extent feasible, avoid excessive exercise and heat exposure [see Overdosage (10.2)].

5.3 Acute Glaucoma

Atropine should be administered with caution in individuals at risk for acute glaucoma.

5.4 Urinary Retention

Atropine should be administered with caution in individuals with clinically significant bladder outflow obstruction because of the risk of urinary retention.

5.5 Pyloric Stenosis

Atropine should be administered with caution in individuals with partial pyloric stenosis because of the risk of complete pyloric obstruction.

5.6 Exacerbation of Chronic Lung Disease

Atropine may cause inspiration of bronchial secretions and formation of dangerous viscid plugs in individuals with chronic lung disease. Respiratory status should be monitored in individuals with chronic lung disease following administration of ATNAA.

6 ADVERSE REACTIONS

The following serious adverse reactions are described elsewhere in the labeling:

- Cardiovascular Risks [see Warnings and Precautions (5.1)]
- Heat Injury [see Warnings and Precautions (5.2)]
- Acute Glaucoma [see Warnings and Precautions (5.3)]
- Urinary Retention [see Warnings and Precautions (5.4)]
- Pyloric Stenosis [see Warnings and Precautions (5.5)]
- Exacerbation of Chronic Lung Disease [see Warnings and Precautions (5.6)]

The following adverse reactions associated with the use of atropine and pralidoxime chloride were identified in the literature. Because these reactions are reported voluntarily from a population of uncertain size, it is not always possible to reliably estimate their frequency or establish a causal relationship to drug exposure.

6.1 Atropine

Because ATNAA contains pralidoxime chloride, which may potentiate the effect of atropine, signs of atropinization may occur earlier than might be expected when atropine is used alone.

Common adverse reactions of atropine can be attributed to its antimuscarinic action. These include dryness of the mouth, blurred vision, dry eyes, photophobia, confusion, headache, dizziness, tachycardia, palpitations, flushing, urinary hesitancy or retention, constipation, abdominal pain, abdominal distention, nausea and vomiting, loss of libido, and impotence. Anhidrosis may produce heat intolerance and impairment of temperature regulation in a hot environment. Dysphagia, paralytic ileus, acute angle closure glaucoma, maculopapular rash, petechial rash, and scarletiniform rash have also been reported. Adverse cardiac reactions, including arrhythmias and myocardial infarction, have been reported with atropine [see Warnings and Precautions (5.1) and Clinical Pharmacology (12.2)].

Larger doses of atropine may produce central nervous system effects such as restlessness, tremor, fatigue, locomotor difficulties, delirium, and hallucinations [see Overdosage (10.1)].

Hypersensitivity reactions will occasionally occur; these are usually seen as skin rashes, and may progress to exfoliation. Anaphylactic reaction and laryngospasm are rare.

6.2 Pralidoxime Chloride

Pralidoxime chloride can cause blurred vision, diplopia and impaired accommodation, dizziness, headache, drowsiness, nausea, tachycardia, increased systolic and diastolic blood pressure [see Clinical Pharmacology 12.2)], muscular weakness, dry mouth, emesis, rash, dry skin, hyperventilation, decreased renal function, and decreased sweating when given parenterally to normal adult volunteers who have not been exposed to anticholinesterase poisons.

In several cases of organophosphorus poisoning, excitement and manic behavior have occurred immediately following recovery of consciousness, in either the presence or absence of pralidoxime chloride administration. However, similar behavior has not been reported in subjects given pralidoxime chloride in the absence of organophosphorus poisoning.

Elevations in AST and/or ALT enzyme levels were observed in 1 of 6 normal adult volunteers given 1200 mg of pralidoxime chloride intramuscularly, and in 4 of 6 adult volunteers given 1800 mg intramuscularly. Levels returned to normal in about two weeks. Transient elevations in creatine kinase were observed in all normal volunteers given the drug.

6.3 Injection Site

Muscle tightness and pain may occur at the injection site.

6.4 Inadvertent Injection

In cases where ATNAA is inadvertently administered to service members who are not poisoned with susceptible organophosphorus nerve agents having anticholinesterase activity, the following effects on their ability to function normally may occur.

Atropine 2 mg IM, roughly the equivalent of one ATNAA injection, when given to healthy male volunteers, is associated with minimal effects on visual, motor, and mental functions, though unsteadiness walking and difficulty concentrating may occur. Atropine reduces body sweating and increases body temperature, particularly with exercise and under hot conditions.

Atropine 4 mg IM, roughly the equivalent of two ATNAA injections, when given to healthy male volunteers, is associated with impaired visual acuity, visual near point accommodation, logical reasoning, digital recall, learning, and cognitive reaction time. Ability to read is reduced or lost. Subjects are unsteady and need to concentrate on walking. These effects begin about 15 minutes to one hour or more post-dose.

Atropine 6 mg IM, roughly the equivalent of three ATNAA injections, when given to healthy male volunteers, is associated with the effects described above plus additional central effects including poor coordination, poor attention span, and visual hallucinations (colored flashes) in many subjects. Frank visual hallucinations, auditory hallucinations, disorientation, and ataxia occur in some subjects. Skilled and labor-intense tasks are performed more slowly and less efficiently. Decision making takes longer and is sometimes impaired.

It is unclear if the above data, obtained from studies of healthy male subjects, can be extrapolated to other populations. In the elderly and individuals with co-morbid conditions, the effects of ≥2 mg atropine on the ability to see, walk, and think properly are unstudied; effects may be greater in susceptible populations.

Service members who are mistakenly injected with ATNAA should avoid potentially dangerous overheating, avoid vigorous physical activity, and seek medical attention as soon as feasible.

7 DRUG INTERACTIONS

7.1 Succinylcholine and Mivacurium

Since pralidoxime chloride in ATNAA reactivates cholinesterases and succinylcholine and mivacurium are metabolized by cholinesterases, service members poisoned by susceptible organophosphorus nerve agents having anticholinesterase activity who have received ATNAA may exhibit accelerated reversal of the neuromuscular blocking effects of succinylcholine and mivacurium (relative to poisoned service member who has not received pralidoxime). Monitor for neuromuscular effects with concomitant administration.

8 USE IN SPECIFIC POPULATIONS

8.1 Pregnancy

Risk Summary

Atropine readily crosses the placental barrier and enters fetal circulation. There are no adequate data on the developmental risk associated with the use of atropine, pralidoxime chloride, or the combination in pregnant women. Adequate animal reproduction studies have not been conducted with atropine, pralidoxime chloride, or the combination. In the U.S. general population, the estimated background risk of major birth defects and miscarriage in clinically recognized pregnancies is 2-4% and 15-20%, respectively.

8.2 Lactation

Risk Summary

Atropine has been reported to be excreted in human milk. It is not known whether pralidoxime chloride is excreted in human milk. There are no data on the effects of atropine or pralidoxime chloride on the breastfed infant or the effects of the drugs on milk production. The developmental and health benefits of breastfeeding should be considered along with the mother's clinical need for ATNAA and any potential adverse effects on the breastfed infant from ATNAA or from the underlying maternal condition.

8.4 Pediatric Use

Safety and effectiveness of ATNAA in pediatric patients have not been established.

8.5 Geriatric Use

Geriatric individuals may be more susceptible to the effects of atropine [see Clinical Pharmacology (12.3)].

8.6 Renal Impairment

Pralidoxime chloride can cause decreased renal function [see Adverse Reactions (6.2)]. Individuals with severe renal impairment may require less frequent doses after the initial dose.

8.7 Hepatic Impairment

Individuals with severe hepatic impairment may require less frequent doses after the initial dose.

10 OVERDOSAGE

10.1 Symptoms

Atropine

Manifestations of atropine overdose are dose-related and include flushing, dry skin and mucous membranes, tachycardia, widely dilated pupils that are poorly responsive to light, blurred vision, and fever (which can sometimes be dangerously elevated). Locomotor difficulties, disorientation, hallucinations, delirium, confusion, agitation, coma, and central depression can occur and may last 48 hours or longer. In instances of severe atropine intoxication, respiratory depression, coma, circulatory collapse, and death may occur.

Pralidoxime Chloride

It may be difficult to differentiate adverse events caused by pralidoxime chloride from those caused by organophosphorus nerve agent poisoning. Symptoms of pralidoxime chloride overdose may include dizziness, blurred vision, diplopia, headache, impaired accommodation, nausea, and tachycardia. Transient hypertension caused by pralidoxime chloride may last several hours.

10.2 Treatment

For atropine overdose, supportive treatment should be administered. If respiration is depressed, artificial respiration with oxygen is necessary. Ice bags, a hypothermia blanket, or other methods of cooling may be required to reduce atropine-induced fever, especially in pediatric patients [see Use in Specific Populations (8.4)]. Catheterization may be necessary if urinary retention occurs. Since atropine elimination largely takes place through the kidney, urinary output must be maintained and increased if possible; intravenous fluids may be indicated. Because of atropine-induced photophobia, the room should be darkened.

A benzodiazepine may be needed to control marked excitement and convulsions. However, large doses for sedation should be avoided because the central nervous system depressant effect may coincide with the depressant effect occurring late in severe atropine poisoning. Barbiturates are potentiated by the anticholinesterases; therefore, barbiturates should be used cautiously in the treatment of convulsions. Central nervous system stimulants are not recommended.

11 DESCRIPTION

Each prefilled ATNAA is a single-dose autoinjector that provides an intramuscular dose of atropine, a cholinergic muscarinic antagonist, and pralidoxime chloride, a cholinesterase reactivator, in a self-contained unit, specifically designed for automatic self- or buddy-administration by military personnel.

When activated, each ATNAA injection delivers the following:

- 2.1 mg of atropine in 0.7 mL of sterile, pyrogen-free solution containing 12.47 mg glycerin, not more than 2.8 mg phenol, 3.05 mg sodium citrate dihydrate, 3.5 mg citric acid monohydrate, and Water for Injection. The pH range is 4.0 – 5.0.
- 600 mg of pralidoxime chloride equivalent to 476.6 mg of pralidoxime in 2 mL of sterile, pyrogen-free solution containing 40 mg benzyl alcohol, 22.5 mg glycine, and Water for Injection. The pH is adjusted with hydrochloric acid. The pH range is 2.0 – 3.0.

After ATNAA has been activated, the empty autoinjector should be disposed of properly [see Dosage and Administration (2.2)]. It cannot be refilled, nor can the protruding needle be retracted.

Atropine occurs as white crystals, usually needle-like, or as a white, crystalline powder. It is slightly soluble in water with a molecular weight of 289.38. Atropine, a naturally occurring belladonna alkaloid, is a racemic mixture of equal parts of d- and l-hyoscyamine, with activity due almost entirely to the levo isomer of the drug.

Chemically, atropine is designated as 1αH,5αH-Tropan-3α-ol (±)-tropate. Its empirical formula is C17H23NO3 and its structural formula is as follows:

Pralidoxime chloride is an odorless, white to pale-yellow crystalline powder, freely soluble in water, with a molecular weight of 172.61. Chemically, pralidoxime chloride is designated as 2-formyl-1-methylpyridinium chloride oxime. Its empirical formula is C7H9CIN2O and its structural formula is indicated above.

12 CLINICAL PHARMACOLOGY

12.1 Mechanism of Action

Atropine

Atropine competitively blocks the effects of acetylcholine, including excess acetylcholine due to organophosphorus nerve agent poisoning, at muscarinic cholinergic receptors on smooth muscle, cardiac muscle, secretory gland cells, and in peripheral autonomic ganglia and the central nervous system.

Pralidoxime Chloride

Pralidoxime chloride reactivates acetylcholinesterase which has been inactivated by phosphorylation due to susceptible organophosphorus nerve agents having anticholinesterase activity . However, pralidoxime chloride does not reactivate acetylcholinesterase inactivated by all organophosphorus nerve agents (e.g. soman). Pralidoxime chloride cannot reactivate phosphorylated acetylcholinesterases that have undergone a further chemical reaction known as "aging." Reactivated acetylcholinesterase hydrolyzes excess acetylcholine resulting from organophosphorus nerve agent poisoning to help restore impaired cholinergic neural function. Reactivation is clinically important because only a small proportion of active acetylcholinesterase is needed to maintain vital functions.

12.2 Pharmacodynamics

Atropine

Atropine reduces secretions in the mouth and respiratory passages, relieves airway constriction, and may reduce centrally-mediated respiratory paralysis. In severe organophosphorus nerve agent poisoning, a fully atropinized patient may develop or continue to have respiratory failure and may require artificial respiration and suctioning of airway secretions. Atropine may cause thickening of secretions.

Atropine-induced parasympathetic inhibition may be preceded by a transient phase of stimulation, especially on the heart where small doses first slow the rate before characteristic tachycardia develops due to paralysis of vagal control. Atropine increases heart rate and reduces atrioventricular conduction time. Adequate atropine doses can prevent or abolish bradycardia or asystole produced by organophosphorus nerve agents.

Atropine may decrease the degree of partial heart block which can occur after organophosphorus poisoning. In some patients with complete heart block, atropine may accelerate the idioventricular rate; in others, the rate is stabilized. In some patients with conduction defects, atropine may cause paradoxical atrioventricular (A-V) block and nodal rhythm.

Atropine will not act on the neuromuscular junction and has no effect on muscle paralysis or weakness, fasciculations or tremors; pralidoxime is intended to treat these symptoms.

Systemic doses of atropine slightly raise systolic and lower diastolic pressures and can produce significant postural hypotension. Such doses also slightly increase cardiac output and decrease central venous pressure. Atropine can dilate cutaneous blood vessels, particularly the "blush" area (atropine flush), and may inhibit sweating, thereby causing hyperthermia, particularly in a warm environment or with exercise [see Warnings and Precautions(5.2)].

Pralidoxime Chloride

Pralidoxime chloride has its most critical effect in relieving respiratory muscle paralysis. Because pralidoxime chloride is less effective in relieving depression of the respiratory center, atropine is always required concomitantly to block the effect of accumulated acetylcholine at this site. Pralidoxime chloride has a minor role in relieving muscarinic signs and symptoms, such as salivation or bronchospasm.

ATNAA temporarily increases blood pressure, a known effect of pralidoxime chloride. In a study of 24 healthy young adults administered a single dose of atropine and pralidoxime chloride auto-injector intramuscularly (approximately 9 mg/kg pralidoxime chloride), diastolic blood pressure increased from baseline by 11 ± 14 mm Hg (mean ± SD), and systolic blood pressure increased by 16 ± 19 mm Hg, at 15 minutes post-dose. Blood pressures remained elevated at these approximate levels through one hour post-dose, began to decrease at two hours post-dose, and were near pre-dose baseline at four hours post-dose.

12.3 Pharmacokinetics

Atropine

Atropine is well absorbed after intramuscular administration. Single dose ATNAA pharmacokinetic data for atropine are shown in Figure 1. The intramuscular injection site was the antero-lateral thigh.

Mean atropine plasma concentrations shown in Figure 1 indicate a plateau beginning at about 5 minutes post-dose and extending through 60 minutes post-dose.

Figure 1. Mean Atropine Plasma Concentrations After a Single ATNAA Intramuscular Injection in 24 Healthy Adult Subjects [Men (N=12), Women (N=12)]

Pralidoxime Chloride

Pralidoxime chloride is well absorbed after intramuscular injection. ATNAA single dose pharmacokinetic data for pralidoxime chloride 600 mg are provided in Figure 2.

Figure 2. Mean Pralidoxime Plasma Concentrations After a Single ATNAA Intramuscular Injection in 24 Healthy Adult Subjects [Men (N=12), Women (N=12)]

The pharmacokinetic properties of the components of ATNAA are presented in Table 2.

Table 2. Pharmacokinetic Properties of the Components of ATNAA Following Intramuscular Administration in Healthy Subjects
Pharmacokinetics related to: | Atropine | Pralidoxime
Absorption
Cmax (mean ± standard deviation) | 13 ± 3 ng/mL | 7 ± 3 mcg/mL
Tmax (mean ± standard deviation) | 31 ± 30 minutes | 28 ± 15 minutes
Distribution
Protein binding | 14 to 22% to plasma proteins | Not appreciably bound to serum proteins
Elimination
T½ | 2.4 ± 0.3 hours | 2 ± 1 hours
Major route of excretion | Urinary | Urinary
Percentage of dose excreted in urine | 50 to 60% as unchanged drug. About 17 to 28% eliminated in the first 100 minutes. | 72 to 94% as unchanged drug. About 57 to 70% eliminated in the first 30 minutes, partly as metabolite.

Specific Populations

Renal and Hepatic Impairment

The pharmacokinetics of atropine or pralidoxime have not been evaluated in subjects with renal or hepatic impairment.

Gender

Atropine: ATNAA AUC0-inf and Cmax values for atropine are 15% higher in females than males. The half-life of atropine is approximately 20 minutes shorter in females than males.

Pralidoxime Chloride: A single ATNAA injection produced a mean Cmax for pralidoxime is about 36% higher in females than males. Tmax is 23 minutes in females and 32 minutes in males. Pralidoxime half-life in males and females are 153 and 107 minutes, respectively.

Geriatric

Atropine: Half-life of intravenous atropine is 3.0 ± 0.9 hours in adults and 10.0 ± 7.3 hours in geriatric patients (65-75 years of age).

13 NONCLINICAL TOXICOLOGY

13.1 Carcinogenesis, Mutagenesis, Impairment of Fertility

Carcinogenesis

ATNAA is indicated for short-term emergency use only, and no adequate studies regarding the carcinogenic potential of atropine or pralidoxime chloride have been conducted.

Mutagenesis

Studies to assess the mutagenic potential of atropine or pralidoxime chloride have not been conducted.

Impairment of Fertility

Atropine:

In studies in which male rats were orally administered atropine (62.5 to 125 mg/kg) for one week prior to mating and throughout a 5-day mating period with untreated females, a dose-related decrease in fertility was observed. A no-effect dose for male reproductive toxicity was not established. The lowest dose tested was 290 times (on a mg/m^2 basis) the dose of atropine in a single application of ATNAA (2.1 mg).

Fertility studies of atropine in females have not been conducted.

Pralidoxime Chloride:

The effects of pralidoxime chloride on fertility have not been assessed.

16 HOW SUPPLIED/STORAGE AND HANDLING

Each single-dose ATNAA autoinjector contains atropine (2.1 mg/0.7 mL; colorless to yellow solution, visible in front chamber) and pralidoxime chloride (600 mg/2mL, equivalent to pralidoxime 476.6 mg/2 mL; colorless to yellow solution, not visible in rear chamber). ATNAA, NDC-11704-777-01, is supplied through the Directorate of Medical Materiel, Defense Supply Center, Philadelphia.

Each ATNAA is supplied in a pouch that provides protection from light.

STORAGE AND HANDLING

Store between 20ºC to 25ºC (68 ºF to 77ºF); excursions permitted between 15ºC and 30ºC (between 59ºF and 86ºF) [See USP Controlled Room Temperature]. Not made with natural rubber latex. Keep from freezing. Protect from light.

17 PATIENT COUNSELING INFORMATION

Use by Military Personnel

ATNAA is intended for use by Military Personnel. See the illustrated Instruction Sheet for Military Personnel.

Seek Definitive Medical Care

If feasible and appropriate, advise service member that ATNAA is an initial emergency treatment, that they need additional care at a healthcare facility.

Avoid Overheating

If feasible and appropriate, advise the service member to avoid a hot environment and excessive physical activity since ATNAA can inhibit sweating which can lead to overheating and heat injury.

Manufactured by:
Meridian Medical Technologies®, LLC
St. Louis, MO 63146

Distributed by:
Defense Logistics Agency Troop Support, Philadelphia
Medical Directorate
700 Robbins Ave
Philadelphia, PA 19111

Manufactured for:
U.S. Army Medical Research and Development Command
ATTN: FCMR-ORA
1430 Veterans Drive
Fort Detrick, MD 21702-5012

07/2022

INSTRUCTIONS FOR USE

Instruction Sheet for Military Personnel

Revised: 5/2020

PRINCIPAL DISPLAY PANEL - Kit Carton Label

ANTIDOTE TREATMENT
NERVE AGENT, AUTO-INJECTOR

For Use in Nerve Agent Poisoning Only

(atropine and pralidoxime chloride injection) Each single-dose auto-injector
delivers an intramuscular injection of 2.1 mg/0.7 mL of atropine and
600 mg/2 mL of pralidoxime chloride equivalent to 476.6 mg pralidoxime.

Distributed by: Defense
Logistics Agency Troop
Support, Philadelphia
Medical Directorate
Manufactured for: U.S.
Army Medical Research
and Development
Command, by Meridian
Medical Technologies,LLC

1
2
3
10 SECONDS

ATNAA Utilizes
Binaject® Technology
0002163

Sterile Solution for Intramuscular Use Only

NSN 6505-01-362-7427

Rx Only

Store at 25°C (77°F); excursions
permitted to 15 - 30°C (59 - 86°F).
Keep From Freezing. Protect From Light.